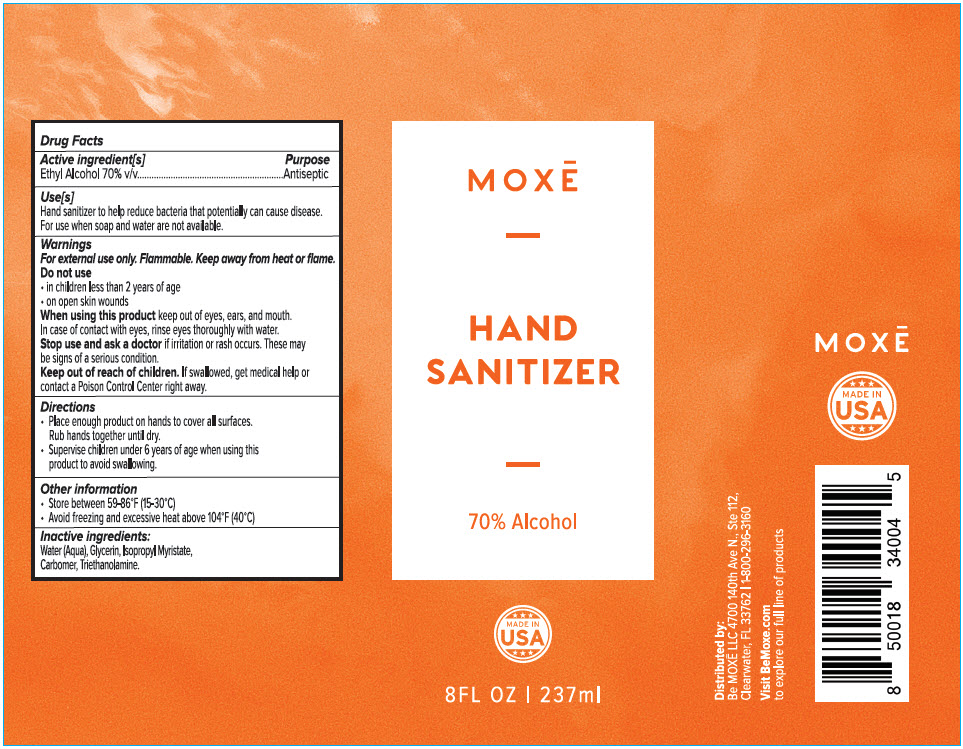 DRUG LABEL: HAND SANITIZER
NDC: 75435-727 | Form: GEL
Manufacturer: Be Moxe, LLC
Category: otc | Type: HUMAN OTC DRUG LABEL
Date: 20220405

ACTIVE INGREDIENTS: Alcohol 70 mL/100 mL
INACTIVE INGREDIENTS: WATER; ISOPROPYL MYRISTATE; CARBOMER HOMOPOLYMER, UNSPECIFIED TYPE; TROLAMINE

HAND SANITIZER

Drug Facts

Active ingredient[s]

Ethyl Alcohol 70% v/v

Purpose

Antiseptic

Use[s]

Hand sanitizer to help reduce bacteria that potentially can cause disease. For use when soap and water are not available.

Warnings

For external use only. Flammable. Keep away from heat or flame.

Do not use

- in children less than 2 years of age
- on open skin wounds

When using this product keep out of eyes, ears, and mouth. In case of contact with eyes, rinse eyes thoroughly with water.

Stop use and ask a doctor if irritation or rash occurs. These may be signs of a serious condition.

Keep out of reach of children. If swallowed, get medical help or contact a Poison Control Center right away.

Directions

- Place enough product on hands to cover all surfaces. Rub hands together until dry.
- Supervise children under 6 years of age when using this product to avoid swallowing.

Other information

- Store between 59-86°F (15-30°C)
- Avoid freezing and excessive heat above 104°F (40°C)

Inactive ingredients

Water (Aqua), Glycerin, Isopropyl Myristate, Carbomer, Triethanolamine.

Distributed by:
Be MOXĒ LLC 4700 140th Ave N., Ste 112,
Clearwater, FL 33762

PRINCIPAL DISPLAY PANEL - 237 ml Bottle Label

MOXĒ

HAND
SANITIZER

70% Alcohol

MADE IN
USA

8FL OZ | 237ml